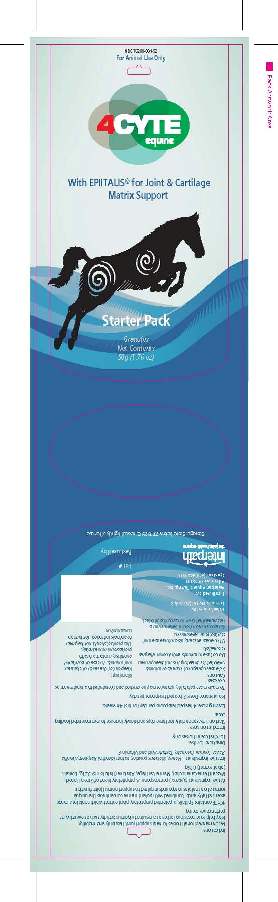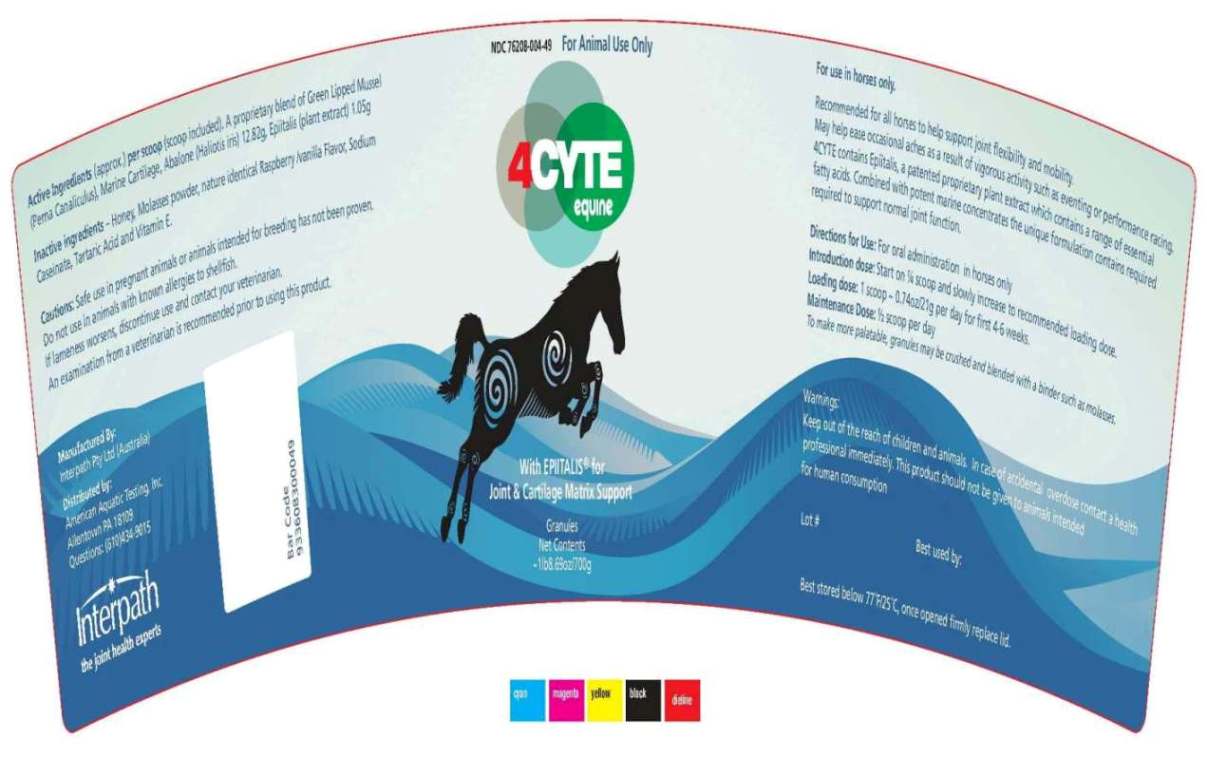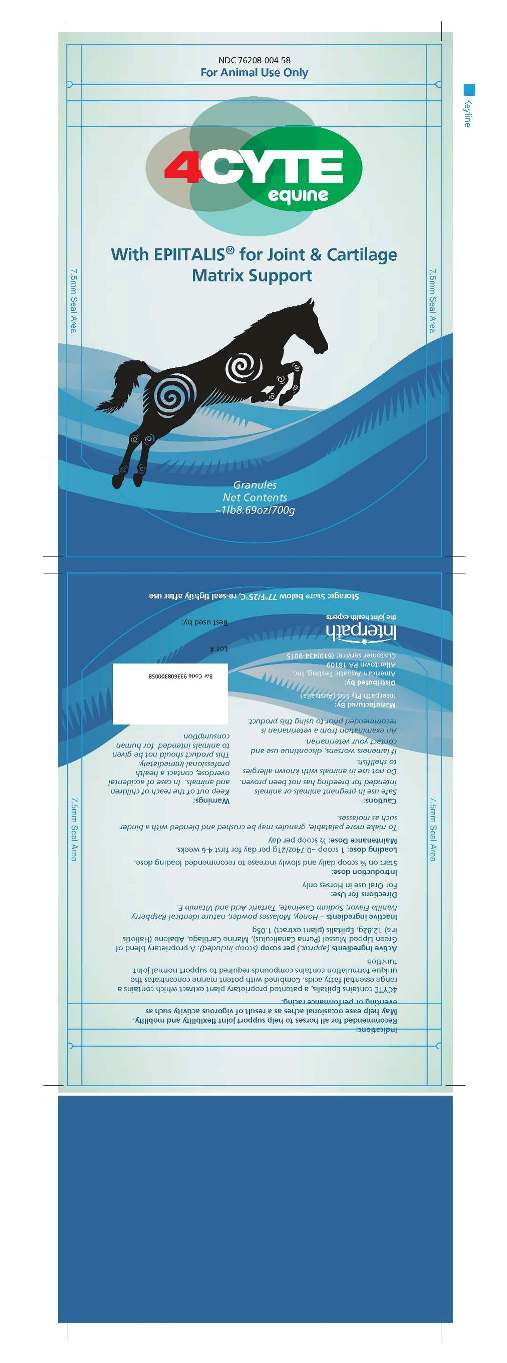 DRUG LABEL: Equine with Epiitalis for Joint and Cartilage Matrix Support
NDC: 76208-004 | Form: GRANULE
Manufacturer: American Aquatic Testing, Inc.
Category: animal | Type: OTC ANIMAL DRUG LABEL
Date: 20110810

ACTIVE INGREDIENTS: NEW ZEALAND GREEN MUSSEL 366 mg/1 g; BLACKFOOT ABALONE 122 mg/1 g; SHARK 122 mg/1 g; PLATYCLADUS ORIENTALIS SEED 50 mg/1 g

4CYTE Equine with EPIITALIS for Joint and Cartilage Matrix Support

Front Panel

NDC 76208-004-52

4CYTE
EQUINEwith
Epiitalis for Joint
and Cartilage Matrix
Support
Starter Pack
Granules
Net Contents
50g (1.76 oz)
Lot #:
Best used by:
Manufactured By:
Interpath Pty Ltd (Australia)
Distributed By:
American Aquatic Testing, Inc.
Allentown, PA 18109
Questions: (610) 434-9015

Active Ingredients

Active Ingredients: per teaspoon
A proprietary blend of Green Lipped
Mussel (Perna Canaliculus),Abalone
(Haliotis iris), Marine Cartilage…………………3.21g
Epiitalis (plant extract) ……………………………0. 26g

Inactive ingredients – Honey, Molasses powder
nature identical Raspberry /vanilla Flavor, Sodium
Caseinate, Tartaric Acid and Vitamin E.

Indications:
Recommended for horses to help support joint
flexibility and mobility.
May help ease occasional aches as a result of
vigorous activity such as eventing or performance racing.

DOSAGE FORMS AND STRENGTHS

Directions for Use:
For oral use in horses only
Introduction dose: Start on 1 teaspoon daily for 3
days and slowly increase to recommended loading dose.
Loading dose: Four (4) heaped teaspoons per day
for first 4-6 weeks
.
Daily Maintenance Dose: Two (2) heaped teaspoons
To make more palatable, granules may be crushed
and blended with a binder such as molasses.

GENERAL PRECAUTIONS

Caution:
Safe use in pregnant animals or animals intended for
breeding has not been proven.
Do not use in animals with known allergies to shellfish.
If lameness worsens, discontinue use and contact your
veterinarian.
An examination from a veterinarian is recommended prior
to using this product.

Warnings:
Keep out of the reach of children and animals.
In case of accidental overdose, contact a health professional
immediately.
This product should not be given to animals intended
for human consumption.

STORAGE AND HANDLING

Storage: Store below 77^0F/25^0C, re-seal tightly after use

PACKAGE LABEL

4CYTE Equine 50g Sachet

PACKAGE LABEL

4CYTE Equine 700g Sachet

PACKAGE LABEL

4CYTE Equine 700g Pail